DRUG LABEL: Fungus Fighter
NDC: 49794-017 | Form: LIQUID
Manufacturer: Continental Manufacturing Chemist, Inc.
Category: animal | Type: OTC ANIMAL DRUG LABEL
Date: 20110322

ACTIVE INGREDIENTS: phenol 0.50 mg/100 mL
INACTIVE INGREDIENTS: alcohol; propylene glycol; water; ORTHOPHENYLPHENOL; POVIDONE K30

Indications:

For use on Cattle, Sheep, Horses, Dogs and other large animals as an aid in the control of ringworm, summer itch, girth itch, foot rot and other fungal infections. Do not use on cats.

Directions for use:

Shake well. Clean the area to be treated, and apply Fungus Fighter directly to the affected area, soaking completely. Let dry. Repeat application daily until condition improves, up to 4 consecutive days. For Foot Rot, apply directly to the affected area, soaking completely. Use daily until condition improves.

Precautions:

Use only as directed. For external animal use only. KEEP OUT OF REACH OF CHILDREN. Avoid contact with eyes and mucous membranes. If irritation develops, or if condition does not improve, discontinue use and consult veterinarian. Not intended for use on animals in commercial food production.

Warning:

Flammable!Keep away from excessive heat or open flame.

Inactive Ingredients:

Ethyl Alcohol, o-Phenylphenol, Polyvinylprrolidone, Propylene Glycol, Purified Water